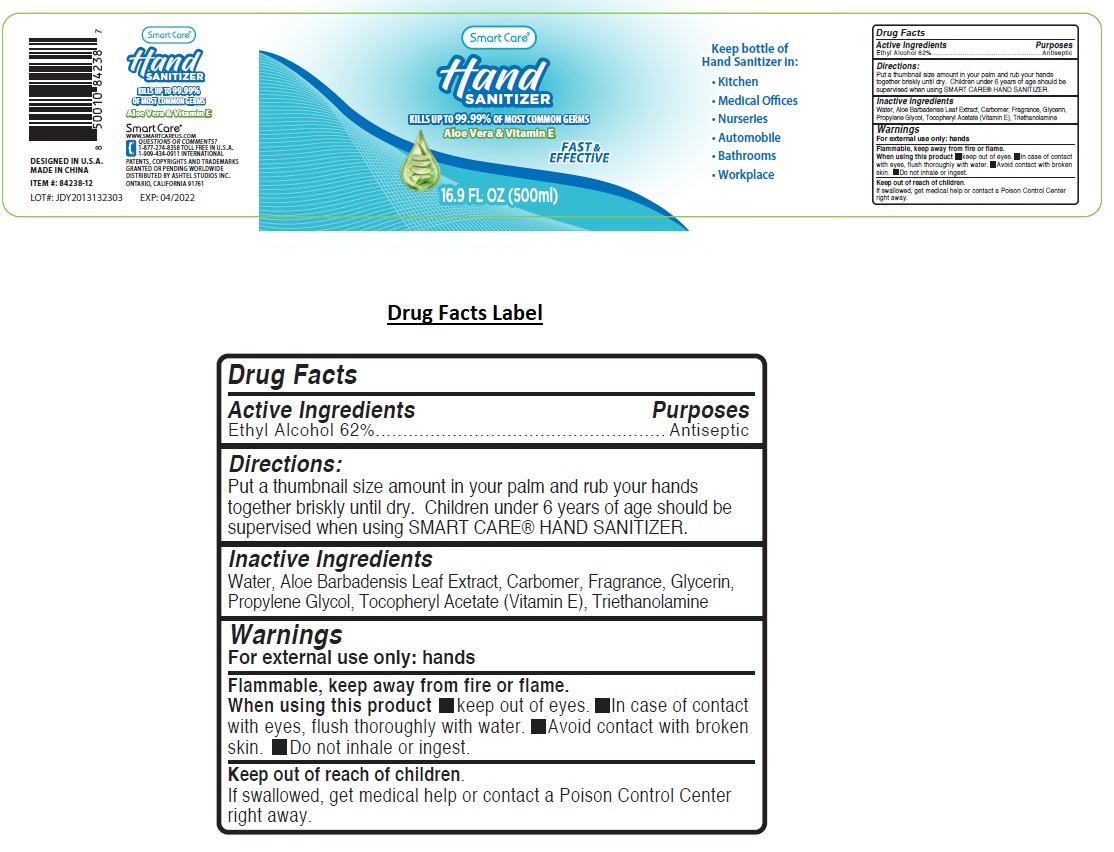 DRUG LABEL: Smart Care Hand Sanitizer 16.9 oz
NDC: 72285-003 | Form: GEL
Manufacturer: Yozzi Co.,ltd
Category: otc | Type: HUMAN OTC DRUG LABEL
Date: 20200423

ACTIVE INGREDIENTS: ALCOHOL 62 mL/100 mL
INACTIVE INGREDIENTS: WATER; ALOE VERA LEAF; CARBOMER HOMOPOLYMER, UNSPECIFIED TYPE; GLYCERIN; PROPYLENE GLYCOL; .ALPHA.-TOCOPHEROL ACETATE; TROLAMINE

Smart Care® Hand SANITIZER

Active Ingredients

Ethyl Alcohol 62%

Purposes

Antiseptic

Uses

For external use only: hands

Directions:

Put a thumbnail size amount in your palm and rub your hands together briskly until dry. Children under 6 years of age should be supervised when using SMART CARE® HAND SANITIZER.

Inactive Ingredients

Water, Aloe Barbadensis Leaf Extract, Carbomer, Fragrance, Glycerin, Propylene Glycol, Tocopheryl Acetate (Vitamin E), Triethanolamine

Warnings:

For external use only: hands

Flammable. Keep away from fire or flame.

When using this product

▪ Keep out of eyes.

▪ In case of contact with eyes, flush thoroughly with water.

▪ Avoid contact with broken skin.

▪ Do not inhale or ingest.

Keep out of reach of children.

If swallowed, get medical help or contact a Poison Control Center right away.

KILLS UP TO 99.99% OF MOST COMMON GERMS

Aloe Vera & Vitamin E

FAST & EFFECTIVE

Keep bottle of Hand Sanitizer in:

- Kitchen
- Medical Offices
- Nurseries
- Automobile
- Bathrooms
- Workplace

DESIGNED IN U.S.A.

MADE IN CHINA

WWW.SMARTCAREUS.COM

QUESTIONS OR COMMENTS?

1-877-274-8358 TOLL FREE IN U.S.A.

1-909-434-0911 INTERNATIONAL

PATENTS, COPYRIGHTS AND TRADEMARKS GRANTED OR PENDING WORLDWIDE

DISTRIBUTED BY ASHTEL STUDIOS INC. ONTARIO, CALIFORNIA 91761

EXP: 04/2022